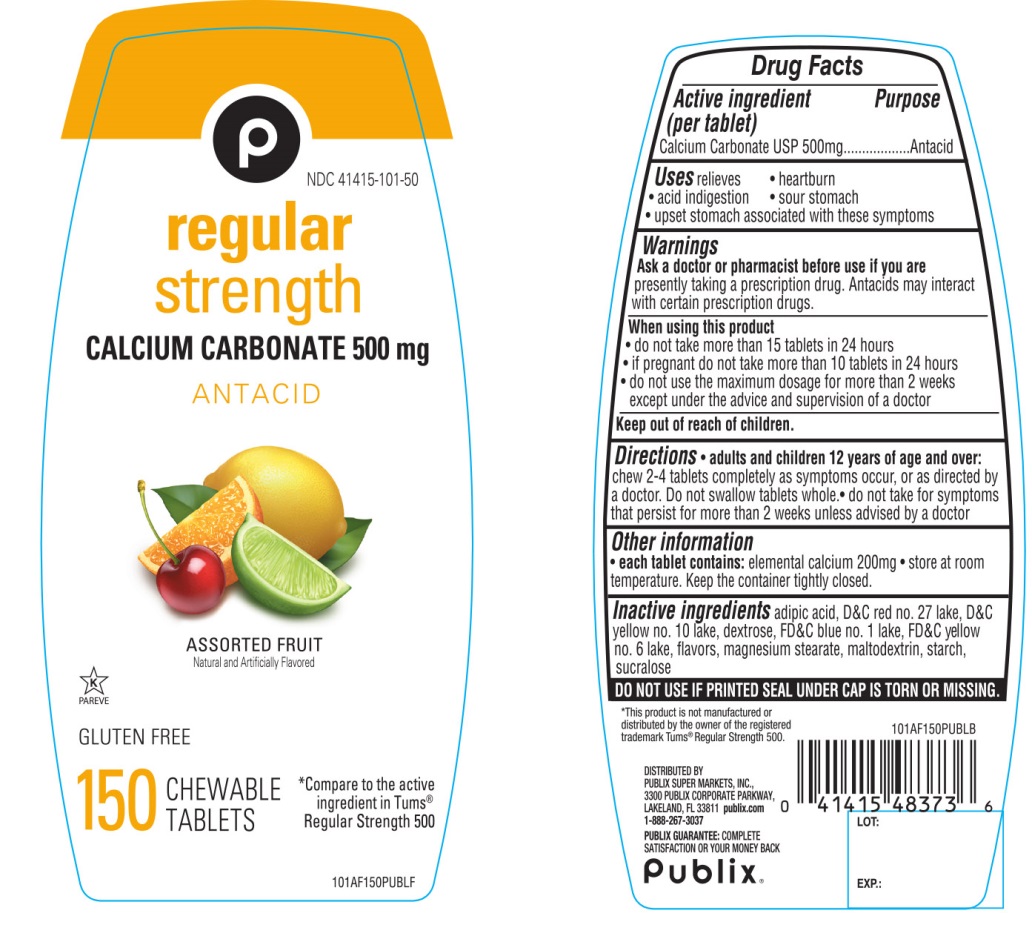 DRUG LABEL: Publix Regular Strength

NDC: 41415-101 | Form: TABLET, CHEWABLE
Manufacturer: PUBLIX SUPER MARKETS, INC
Category: otc | Type: HUMAN OTC DRUG LABEL
Date: 20251028

ACTIVE INGREDIENTS: CALCIUM CARBONATE 500 mg/1 1
INACTIVE INGREDIENTS: ADIPIC ACID; D&C RED NO. 27; D&C YELLOW NO. 10; DEXTROSE, UNSPECIFIED FORM; FD&C BLUE NO. 1; FD&C YELLOW NO. 6; MAGNESIUM STEARATE; MALTODEXTRIN; STARCH, CORN; SUCRALOSE

Publix® Regular Strength Assorted Fruit Antacid Tablets

Active ingredient (per tablet)

Calcium Carbonate USP 500mg

Purpose

Antacid

Uses

relieves

- heartburn
- acid indigestion
- sour stomach
- upset stomach associated with these symptoms

Warnings

Ask a doctor or pharmacist before use if you arepresently taking a prescription drug. Antacids may interact with certain prescription drugs.

When using this product

- do not take more than 15 tablets in 24 hours
- If pregnant do not take more than10 tablets in 24 hours
- do not use the maximum dosage for more than 2 weeks except under the advice and supervision of a doctor.

Directions

- adults and children 12 years and over: chew 2-4 tablets as symptoms occur, or as directed by a doctor. Do not swallow tablets whole.
- do not take for symptoms that persist for more than 2 weeks unless advised by a doctor.

Other information

- each tablet contains:elemental calcium 200 mg
- store at room temperature. Keep the container tightly closed.

Inactive ingredients

adipic acid, D&C red #27 lake, D&C Yellow #10 lake, dextrose, FD&C blue #1 lake, FD&C yellow #6 lake, flavors, magnesium stearate, maltodextrin, starch, sucralose.

Questions or comments?

1-866-267-3037

SAFETY SEALED: DO NOT USE IF PRINTED SEAL UNDER CAP IS TORN OR MISSING.

Package/Label Principal Display Panel

NDC 41415-101-50

Publix®

*Compare to the active ingredient in Tums®Regular Strength 500

Assorted Fruit Flavor

REGULAR STRENGTH

CALCIUM CARBONATE 500 mg

ANTACID

ASSORTED FRUIT

150 CHEWABLE TABLETS

GLUTEN-FREE

K PAREVE

DISTRIBUTED BY:

PUBLIX SUPER MARKETS, INC.,

3300 PUBLIX CORPORATE PARKWAY,

LAKELAND, FL 33811 publix.com

1-888-267-3037

PUBLIX GUARANTEE:COMPLETE SATISFACTION OR YOUR MONEY BACK

*This product is not manufactured or distributed by GlaxoSmithKline LLC, the owner of the registered trademark Tums®Regular Strength 500.